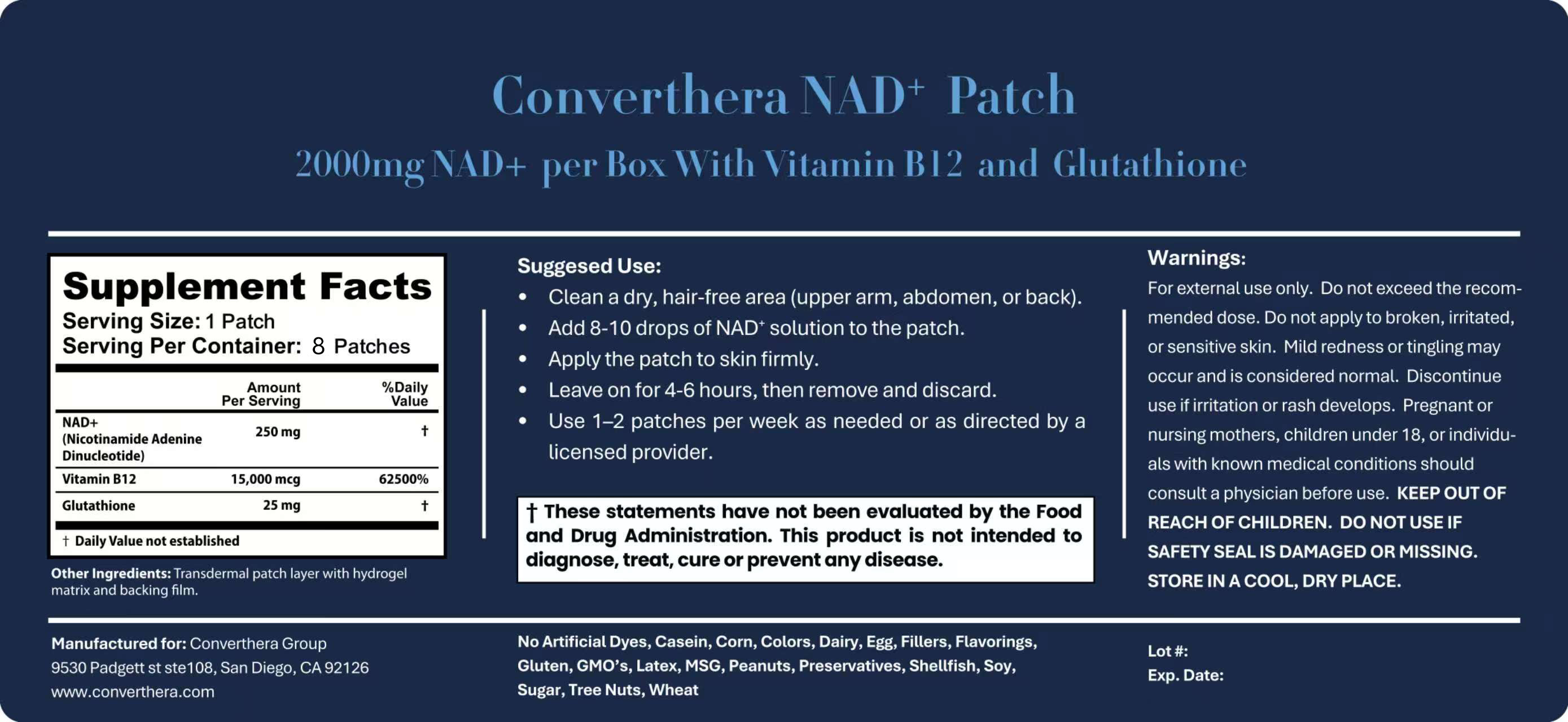 DRUG LABEL: Converthera NAD plus Patch
NDC: 85945-0001 | Form: PATCH
Manufacturer: Through Medical INC.
Category: otc | Type: HUMAN OTC DRUG LABEL
Date: 20250718

ACTIVE INGREDIENTS: NICOTINAMIDE ADENINE DINUCLEOTIDE 250 mg/1 U; GLUTATHIONE 25 mg/1 U
INACTIVE INGREDIENTS: LACTOSE; GLUTENIN

DOSAGE AND ADMINISTRATION

Apply the patch to skin firmly.
Leave on for 4-6 hours, then remove and discard.
Use 1-2 patches per week as needed or as directed by a licensed provider.

Warnings:
For external use only. Do not exceed the recom- mended dose. Do not apply to broken, irritated, or sensitive skin. Mild redness or tingling may occur and is considered normal. Discontinue use if irritation or rash develops. Pregnant or nursing mothers, children under 18, or individu- als with known medical conditions should consult a physician before use. KEEP OUT OF REACH OF CHILDREN. DO NOT USE IF SAFETY SEAL IS DAMAGED OR MISSING. STORE IN A COOL, DRY PLACE.

INACTIVE INGREDIENT

Other Ingredients: Transdermal patch layer with hydrogel matrix and backing film.

INDICATIONS AND USAGE

Clean a dry, hair-free area (upper arm, abdomen, or back).
Add 8-10 drops of NAD+ solution to the patch.
Apply the patch to skin firmly.
Leave on for 4-6 hours, then remove and discard.

KEEP OUT OF REACH OF CHILDREN.

ACTIVE INGREDIENT

NAD+
(Nicotinamide Adenine
250 mg

Dinucleotide)
Vitamin B12
15,000 mcg

Glutathione

PURPOSE

Use 1-2 patches per week as needed or as directed by a licensed provider.

PACKAGE LABEL

Labeling